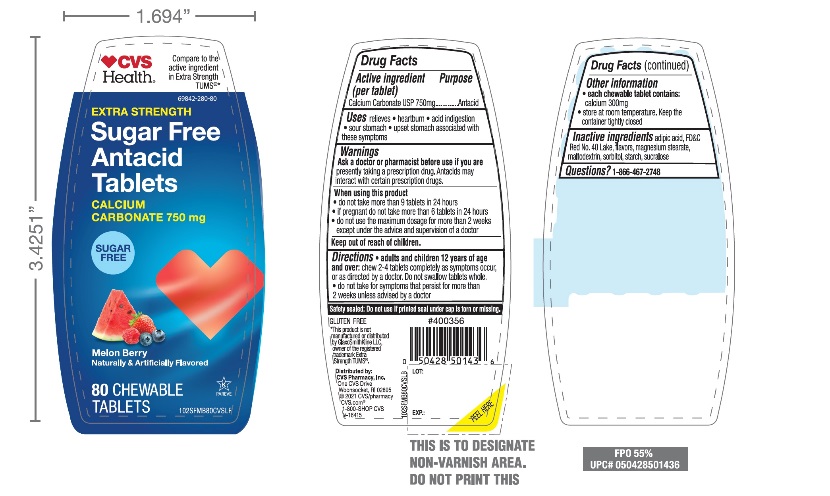 DRUG LABEL: CVS Health Extra Strength

NDC: 69842-280 | Form: TABLET, CHEWABLE
Manufacturer: CVS PHARMACY, INC.
Category: otc | Type: HUMAN OTC DRUG LABEL
Date: 20251204

ACTIVE INGREDIENTS: CALCIUM CARBONATE 750 mg/1 1
INACTIVE INGREDIENTS: ADIPIC ACID; FD&C RED NO. 40; MAGNESIUM STEARATE; MALTODEXTRIN; SORBITOL; STARCH, CORN; SUCRALOSE

CVS Health Extra Strength Sugar Free Antacid Tablets

Active ingredient (per tablet)

Calcium Carbonate USP 750 mg

Purpose

Antacid

Uses

relieves

- heartburn
- acid indigestion
- sour stomach
- upset stomach associated with these symptoms

Warnings

Ask a doctor or pharmacist before use if you are

presently taking a prescription drug. Antacids may interact with certain prescription drugs.

When using this product

- do not take more than 10 tablets in 24 hours
- if pregnant do not take more than 6 tablets in 24 hours
- do not use the maximum dosage for more than 2 weeks except under the advice and supervision of a doctor

Directions

- adults and children 12 years of age and over:chew 2 – 4 tablets completely as symptoms occur, or as directed by a doctor. Do not swallow tablets whole
- do not take for symptoms that persist for more than 2 weeks unless advised by a doctor

Other information

- each chewable tablet contains:elemental calcium 300mg
- Store at room temperature. Keep the container tightly closed.

Inactive ingredients

Adipic acid, FD&C No. 40 Lake, flavors, magnesium stearate, maltodextrin sorbitol, starch, sucralose

Questions?

1-866-467-2748

Principal Display Panel

CVS Health®

Compare to the active ingredient in Extra Strength Tums®*

NDC69842-280-80

EXTRA STRENGTH SUGAR FREE

Antacid Tablets

CALCIUM CARBONATE 750 mg

SUGAR-FREE

Melon Berry

Naturally and Artificially Flavored

80 CHEWABLE TABLETS

Safety sealed – Do not use if printed inner seal beneath cap is missing or broken.

GLUTEN-FREE

Distributed by:

CVS Pharmacy, Inc.

One CVS Drive

Woonsocket, RI 02695

©2021 CVS/Pharmacy®

CVS.com, 1-800-SHOP-CVS